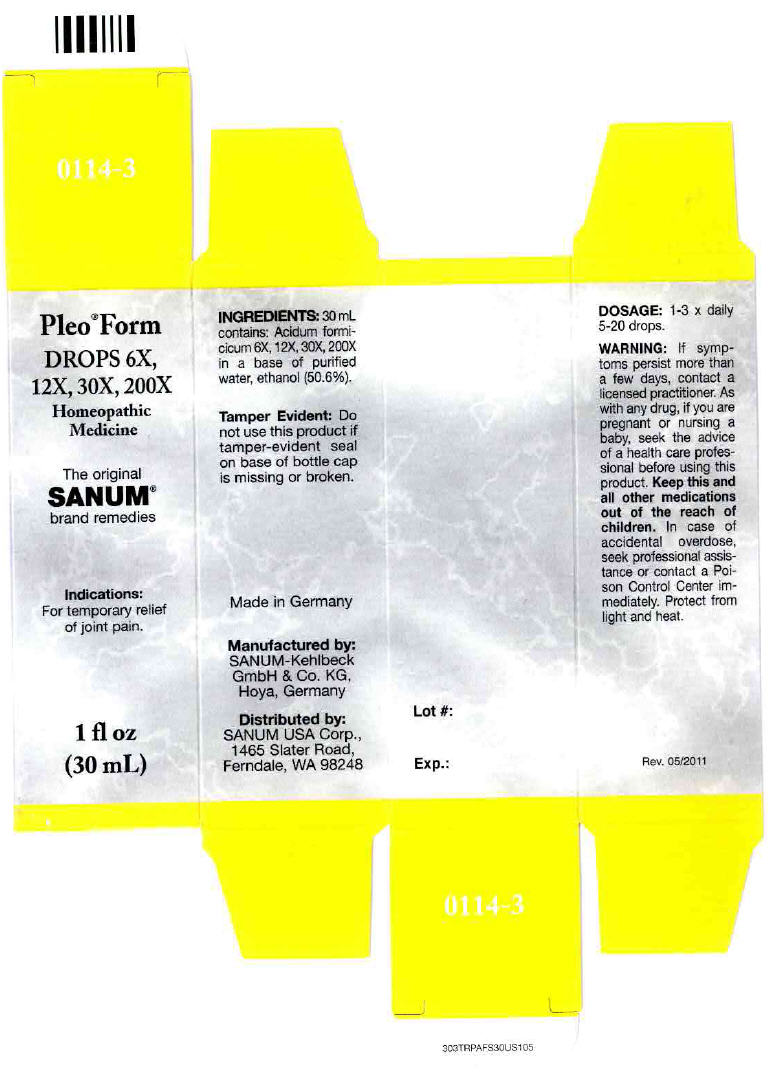 DRUG LABEL: Pleo Form
NDC: 60681-0114 | Form: SOLUTION/ DROPS
Manufacturer: Sanum Kehlbeck GmbH & Co. KG
Category: homeopathic | Type: HUMAN OTC DRUG LABEL
Date: 20120523

ACTIVE INGREDIENTS: formic acid 200 [hp_X]/30 mL
INACTIVE INGREDIENTS: water; alcohol

Pleo™ Form
DROPS 6X,
12X, 30X, 200X

PURPOSE

Homeopathic
Medicine

The original
SANUM®
brand remedies

Indications

For temporary relief of joint pain.

ACTIVE INGREDIENT

INGREDIENTS

30 mL contains: Acidum formicicum 6X, 12X, 30X, 200X in a base of purified water, ethanol (50.6%).

Tamper Evident

Do not use this product if tamper-evident seal on base of bottle cap is missing or broken.

DOSAGE

1-3 × daily 5-20 drops.

WARNING

ASK DOCTOR

If symptoms persist more than a few days, contact a licensed practitioner.

PREGNANCY OR BREAST FEEDING

As with any drug, if you are pregnant or nursing a baby, seek the advice of health care professional before using this product.

KEEP OUT OF REACH OF CHILDREN

Keep this and all other medications out of the reach of children. Incase of accidental overdose, seek professional assistance or contact a Poison Control Center immediately.

STORAGE AND HANDLING

Protect from light and heat.

Manufactured by:
SANUM-Kehlbeck
GmbH & Co. KG,
Hoya, Germany

Distributed by:
SANUM USA Corp.,
1465 Salter Road,
Ferndale, WA 98248

PRINCIPAL DISPLAY PANEL - 30 mL Bottle Carton

Pleo® Form

DROPS 6X,
12X, 30X, 200X
Homeopathic
Medicine

The original
SANUM®
brand remedies

Indications:
For temporary relief
of joint pain.

1 fl oz
(30 mL)